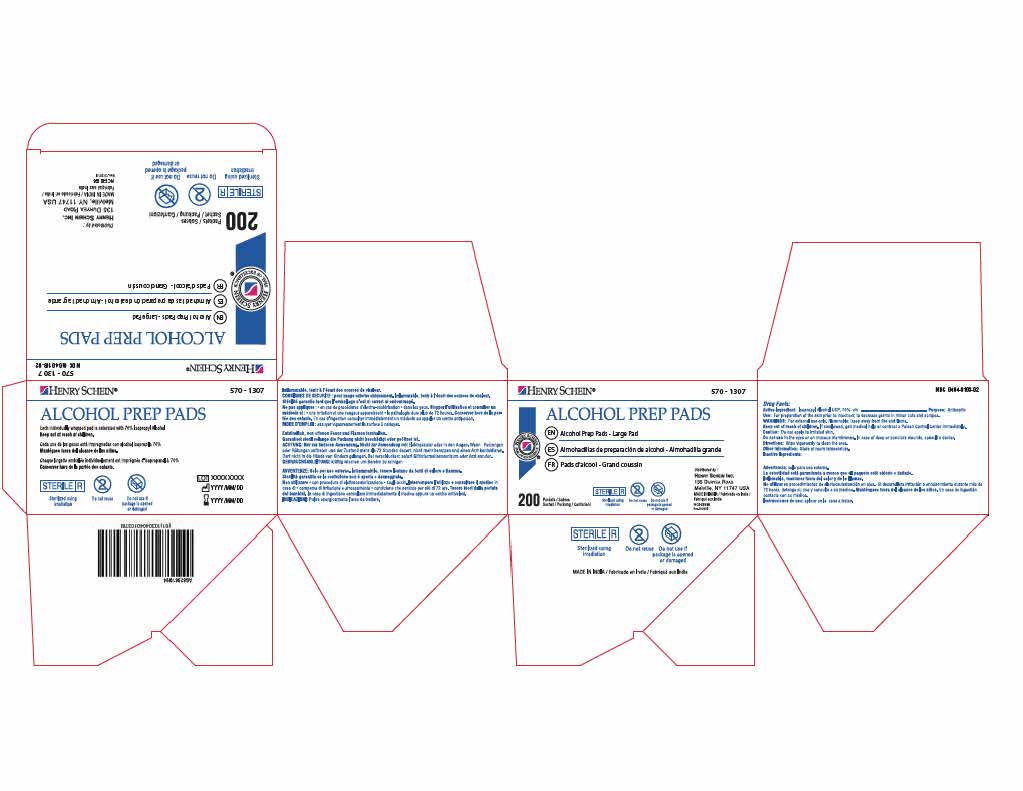 DRUG LABEL: Alcohol Prep Pads
NDC: 0404-0103 | Form: SWAB
Manufacturer: Henry Schein, Inc.
Category: otc | Type: HUMAN OTC DRUG LABEL
Date: 20251023

ACTIVE INGREDIENTS: ISOPROPYL ALCOHOL 70 mL/100 mL
INACTIVE INGREDIENTS: WATER

Henry Schein Large Alcohol Prep Pad

ACTIVE INGREDIENT

Isopropyl Alcohol USP 70% v/v

PURPOSE

Antiseptic

INDICATIONS AND USAGE

For preparation of the skin prior to injection; to decrease germs in minor cuts and scrapes

WARNINGS

For external use only. Flammable; keep away from fire and flame.

KEEP OUT OF REACH OF CHILDREN

If swallowed, get medical help or contact a Poison Control Center immediately.

OTHER SAFETY INFORMATION

Do not apply to irritated skin.

DO NOT USE

In the eyes, or on mucus membranes. In case of deep or puncture wounds, consult a doctor.

DOSAGE AND ADMINISTRATION

Wipe vigorously to clean the area.

STORAGE AND HANDLING

Store at room temperature.

INACTIVE INGREDIENT

Water